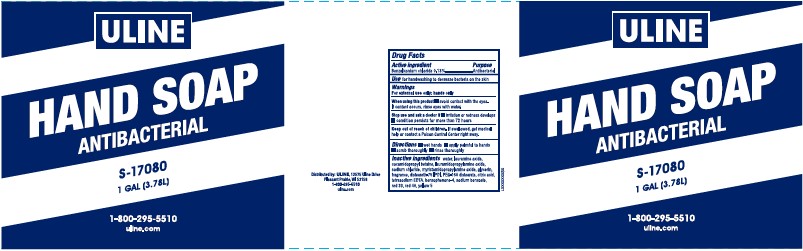 DRUG LABEL: Antibacterial Hand Wash
NDC: 69790-488 | Form: LIQUID
Manufacturer: Uline
Category: otc | Type: HUMAN OTC DRUG LABEL
Date: 20260217

ACTIVE INGREDIENTS: BENZALKONIUM CHLORIDE 1.313 mg/1 mL
INACTIVE INGREDIENTS: WATER; LAURAMINE OXIDE; COCAMIDOPROPYL BETAINE; LAURAMIDOPROPYLAMINE OXIDE; SODIUM CHLORIDE; MYRISTAMIDOPROPYLAMINE OXIDE; GLYCERIN; DISTEARETH-75 ISOPHORONE DIISOCYANATE; PEG-150 DISTEARATE; CITRIC ACID MONOHYDRATE; EDETATE SODIUM; SULISOBENZONE; SODIUM BENZOATE; D&C RED NO. 33; FD&C RED NO. 40; FD&C YELLOW NO. 5

Uline 488.003/488AD
Light Moisturizing Antibacterial Hand Soap

Active ingredient

Benzalkonium chloride 0.13%

Purpose

Antibacterial

Use

for handwashing to decrease bacteria on the skin

Warnings

For external use only: hands only

When using this product

- avoid contact with the eyes. If contact occurs, rinse eyes with water.

Stop use and ask a doctor if

- irritation or redness develops
- condition persists for more than 72 hours

Keep out of reach of children.

If swallowed, get medical help or contact a Poison Control Center right away.

Directions

- wet hands
- apply palmful to hands
- scrub thoroughly
- rinse thoroughly

Inactive ingredients

water, lauramine oxide, cocamidopropyl betaine, lauramidopropylamine oxide, sodium chloride, myristamidopropylamine oxide, glycerin, fragrance, disteareth-75 IPDI, PEG-150 distearate, citric acid, tetrasodium EDTA, benzophenone-4, sodium benzoate, red 33, red 40, yellow 5

ADVERSE REACTION

Distributed by: ULINE, 12575 Uline Drive

Pleasant Prairie, WI 53158

1-800-295-5510

unline.com

principal display panel

ULINE

HAND SOAP

ANTIBACTERIAL

S-17080

1 GAL (3.78 L)

1-800-295-5510

uline.com